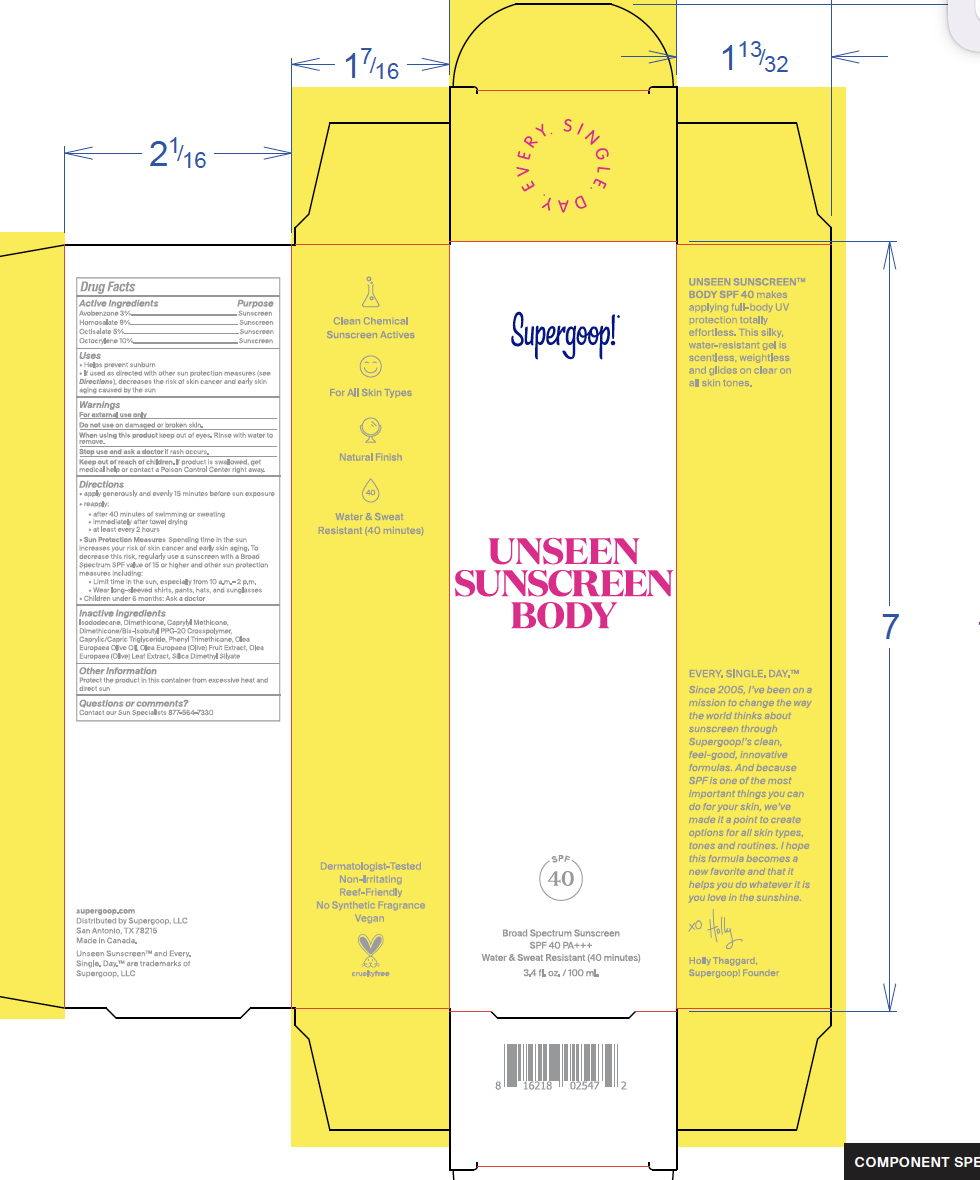 DRUG LABEL: Unseen Sunscreen Body SPF 40
NDC: 75936-605 | Form: LOTION
Manufacturer: Supergoop, LLC
Category: otc | Type: HUMAN OTC DRUG LABEL
Date: 20241205

ACTIVE INGREDIENTS: OCTISALATE 5 g/100 mL; AVOBENZONE 3 g/100 mL; OCTOCRYLENE 10 g/100 mL; HOMOSALATE 9 g/100 mL
INACTIVE INGREDIENTS: DIMETHICONE/BIS-ISOBUTYL PPG-20 CROSSPOLYMER; CAPRYLYL TRISILOXANE; SILICA DIMETHYL SILYLATE; PHENYL TRIMETHICONE; OLEA EUROPAEA FRUIT VOLATILE OIL; OLEA EUROPAEA (OLIVE) OIL UNSAPONIFIABLES; MEDIUM-CHAIN TRIGLYCERIDES; ISODODECANE; OLEA EUROPAEA LEAF

Unseen Sunscreen Body SPF 40

ACTIVE INGREDIENT

Avobenzone 3%

Homosalate 9%

Octisalate 5%

Octocrylene 10%

PURPOSE

Helps prevent sunburn

If used as directed with other sun protection measures (see Directions), decreases the risk of skin cancer and early skin aging caused by the sun

Keep out of reach of children. If product is swallowed, get medical help or contact a Poison Control Center right away.

DOSAGE AND ADMINISTRATION

- apply generously and evenly 15 minutes before sun exposure
- reapply: after 40 minutes of swimming or sweating, immediately after towel drying, at least every 2 hours

• Sun Protection Measures: Spending time in the sun increases your risk of skin cancer and early skin aging. To decrease this risk, regularly use a sunscreen with a Broad Spectrum SPF value of 15 or higher and other sun protection measures including:

Limit time in the sun, especially from 10 a.m. - 2 p.m.

Wear long-sleeved shirts, pants, hats, and sunglasses

Children under 6 months: Ask a doctor

INACTIVE INGREDIENT

Inactive Ingredients: Isododecane, Dimethicone, Caprylyl Methicone, Dimethicone/Bis-Isobutyl PPG-20 Crosspolymer, Caprylic/CapricTriglyceride, Phenyl Trimethicone, Olea Europaea Olive Oil, Olea Europaea (Olive) Fruit Extract, Olea Europaea (Olive) Leaf Extract, Silica Dimethyl Silyate

WARNINGS

For External use only

Do not use on damaged or broken skin

When using this product, Keep out of eyes. Rinse with water to remove.

Stop use and ask a doctor is rash occurs

PACKAGE LABEL

Unseen Sunscreen Body

SPF 40 PA +++

Broad Spectrum Sunscreen

Water and Sweat Resistant (40 minutes)

3.4 fl. oz. / 100 mL